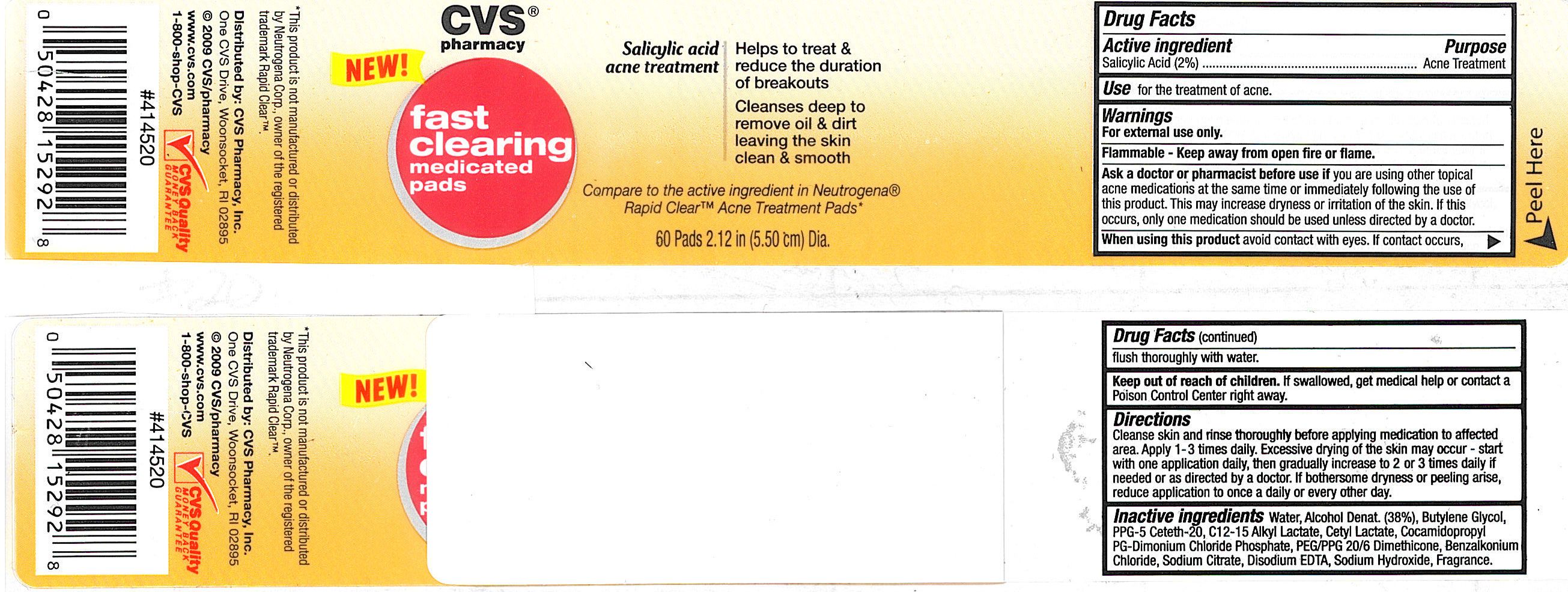 DRUG LABEL: CVS Fast Clearing Medicated Pads
NDC: 59779-076 | Form: SWAB
Manufacturer: CVS PHARMACY
Category: otc | Type: HUMAN OTC DRUG LABEL
Date: 20100713

ACTIVE INGREDIENTS: SALICYLIC ACID 21 mg/1 1
INACTIVE INGREDIENTS: WATER; DOCUSATE SODIUM; CARBOMER HOMOPOLYMER TYPE C; SODIUM HYDROXIDE; EDETATE SODIUM

drug facts

Active ingredient Purpose
Salicylic Acid, (2%).......................................Acne Treatment

Use
- for the treatment of acne

Keep out of reach of children.If swallowed, get medical help or contact a Poison
Control Center right away.

Directions

- cleanse skin and rinse thoroughly before applying medication to affected area.
- Apply 1-3 times daily. Excessive drying of the skin may occur - start with one application daily,
then gradually increase to 2 or 3 times daily if needed or as directed by a doctor.
If bothersome dryness or peeling arise, reduce application to once a daily or every other day.

Warnings
For external use only.
Flammable - Keep away from open fire or flame.
Ask a doctor or pharmacist before use if
you are using other topical acne medications at the same time or immediately
following the use of this product. This may increase dryness or irritation of the
skin. If this occurs, only one medication should be used unless directed by a doctor.
When using this product
- avoid contact with eyes. If contact occurs, flush thoroughly with water.
Stop use and ask a doctor if skin irritation occurs
Keep out of reach of children. If swallowed, get medical help or contact a Poison
Control Center right away.

Directions

- cleanse skin and rinse thoroughly before applying medication to affected area.
- Apply 1-3 times daily. Excessive drying of the skin may occur - start with one application daily,
then gradually increase to 2 or 3 times daily if needed or as directed by a doctor.
If bothersome dryness or peeling arise, reduce application to once a daily or every other day.

INACTIVE INGREDIENT

Inactive Ingredients Water, Alcohol Denat. (38%), Butylene Glycol, PPG-5 Ceteth-20,
c12-15 Alkyl Lactate, Cetyl Lactate, Cocamidopropyl PG-Dimonium Chloride Phosphate,
PEG/PPG 20/6 Dimethicone, Benzalkonium Chloride, Sodium Citrate, Disodium EDTA,
Sodium Hydroxide, Fragrance